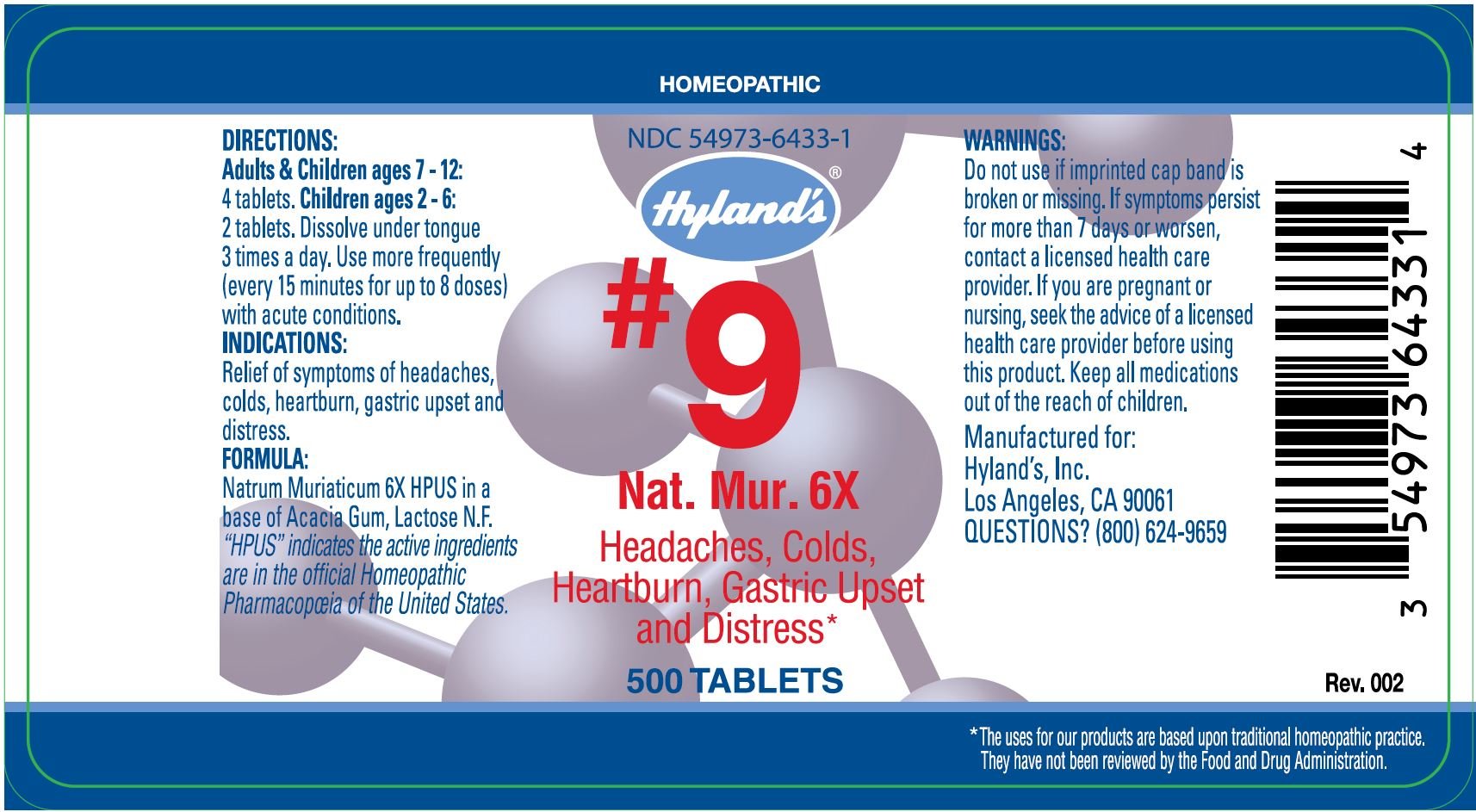 DRUG LABEL: NATRUM MURIATICUM
NDC: 54973-6433 | Form: TABLET
Manufacturer: Hyland's Inc.
Category: homeopathic | Type: HUMAN OTC DRUG LABEL
Date: 20221219

ACTIVE INGREDIENTS: SODIUM CHLORIDE 6 [hp_X]/1 1
INACTIVE INGREDIENTS: ACACIA; LACTOSE

#9 Natrum Muriaticum 6X

DIRECTIONS

Adults & Children ages 7 - 12: 4 tablets. Children ages 2 - 6: 2 tablets. Dissolve under tongue 3 times a day. Use more frequently (every 15 minutes for up to 8 doses) with acute conditions.

INDICATIONS

PURPOSE

Relief of symptoms of headaches, colds,heartburn, gastric upset and distress

FORMULA

Natrum Muriaticum 6X HPUS

INACTIVE INGREDIENT

In a base of Acacia Gum, Lactose N.F.

“HPUS” indicates that the active ingredients are in the official Homeopathic Pharmacopœia of the United States.

Warnings

Do not use if imprinted cap band is broken or missing.

ASK DOCTOR/PHARMACIST

If symptoms persist for more than 7 days or worsen, contact a licensed health care provider.

PREGNANCY OR BREAST FEEDING

If you are pregnant or nursing, seek the advice of a licensed health care provider before using this product.

KEEP OUT OF REACH OF CHILDREN

Keep all medications out of the reach of children.

QUESTIONS?

(800) 624-9659

PRINCIPAL DISPLAY PANEL - 500 Tablet Bottle Label

HOMEOPATHIC

NDC 54973-6433-1

Hyland's®

#9
Nat. Mur. 6X

Headaches, Colds,

Heartburn, Gastric Upset

and Distress*

500 TABLETS